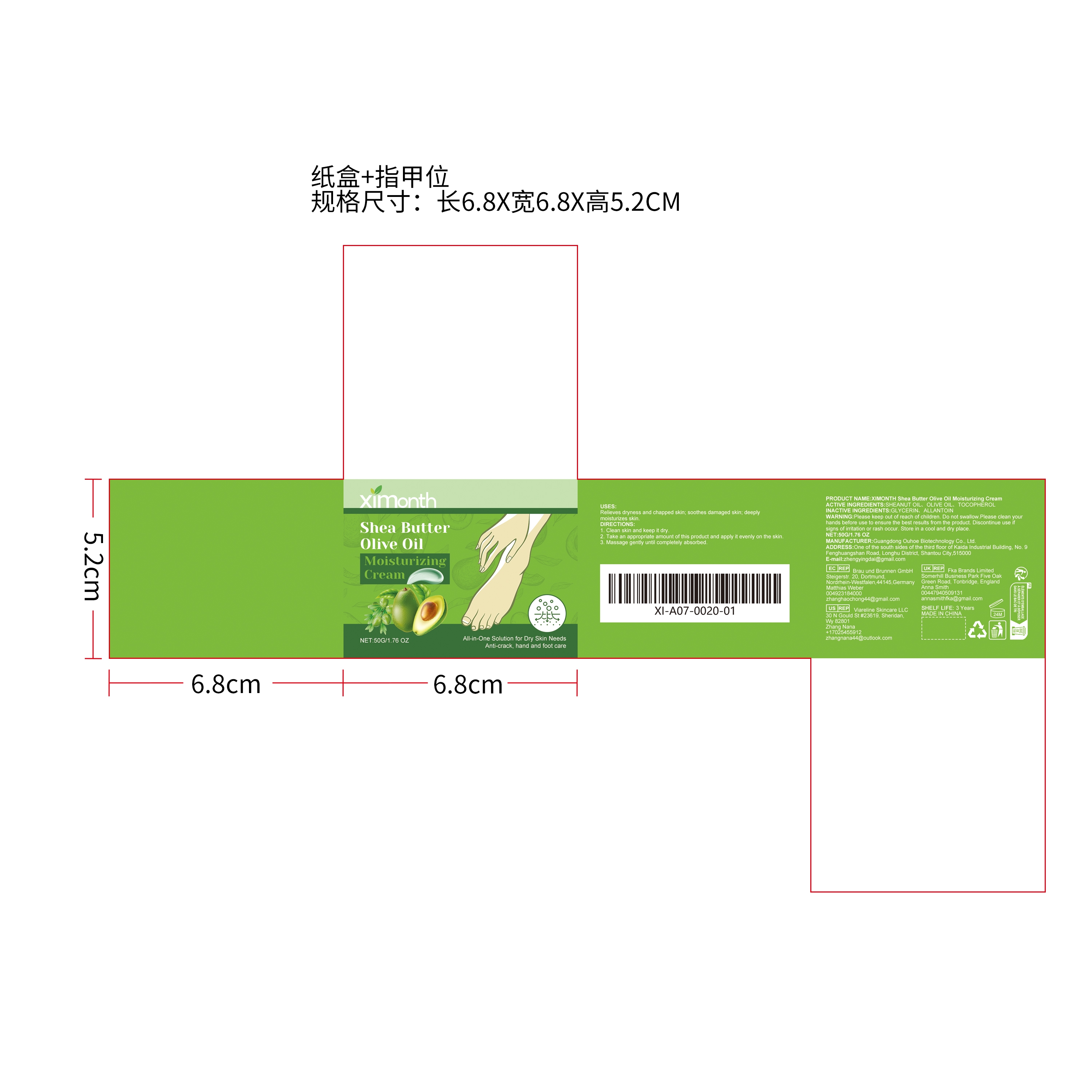 DRUG LABEL: XIMONTH Shea Butter Olive Oil Moisturizing Cream
NDC: 84744-056 | Form: CREAM
Manufacturer: Guangdong Ouhoe Biotechnology Co., Ltd.
Category: otc | Type: HUMAN OTC DRUG LABEL
Date: 20241022

ACTIVE INGREDIENTS: SHEANUT OIL 10 g/50 g; TOCOPHEROL 5 g/50 g; OLIVE OIL 5 g/50 g
INACTIVE INGREDIENTS: ALLANTOIN 10 g/50 g; GLYCERIN 20 g/50 g

Active Ingredient(s)

SHEANUT OIL、OLIVE OIL、TOCOPHEROL

Purpose

Relieves dryness and chapped skin; soothes damaged skin; deeply moisturizes skin.

Use

1. Clean skin and keep it dry.
2. Take an appropriate amount of this product and apply it evenly on the skin.
3. Massage gently until completely absorbed.

Do not use

Discontinue use if signs of irritation or rash occur.

Stop Use

Discontinue use if signs of irritation or rash occur.

KEEP OUT OF REACH OF CHILDREN

Please keep out of reach of children. Do not swallow.

Warnings

Please keep out of reach of children.Do not swallow.Please clean your hands before use to ensure the best results from the product.Discontinue use if signs of irritation or rash occur.Store in a cool and dry place.

STORAGE AND HANDLING

Store in a cool and dry place.

INACTIVE INGREDIENT

GLYCERIN、ALLANTOIN